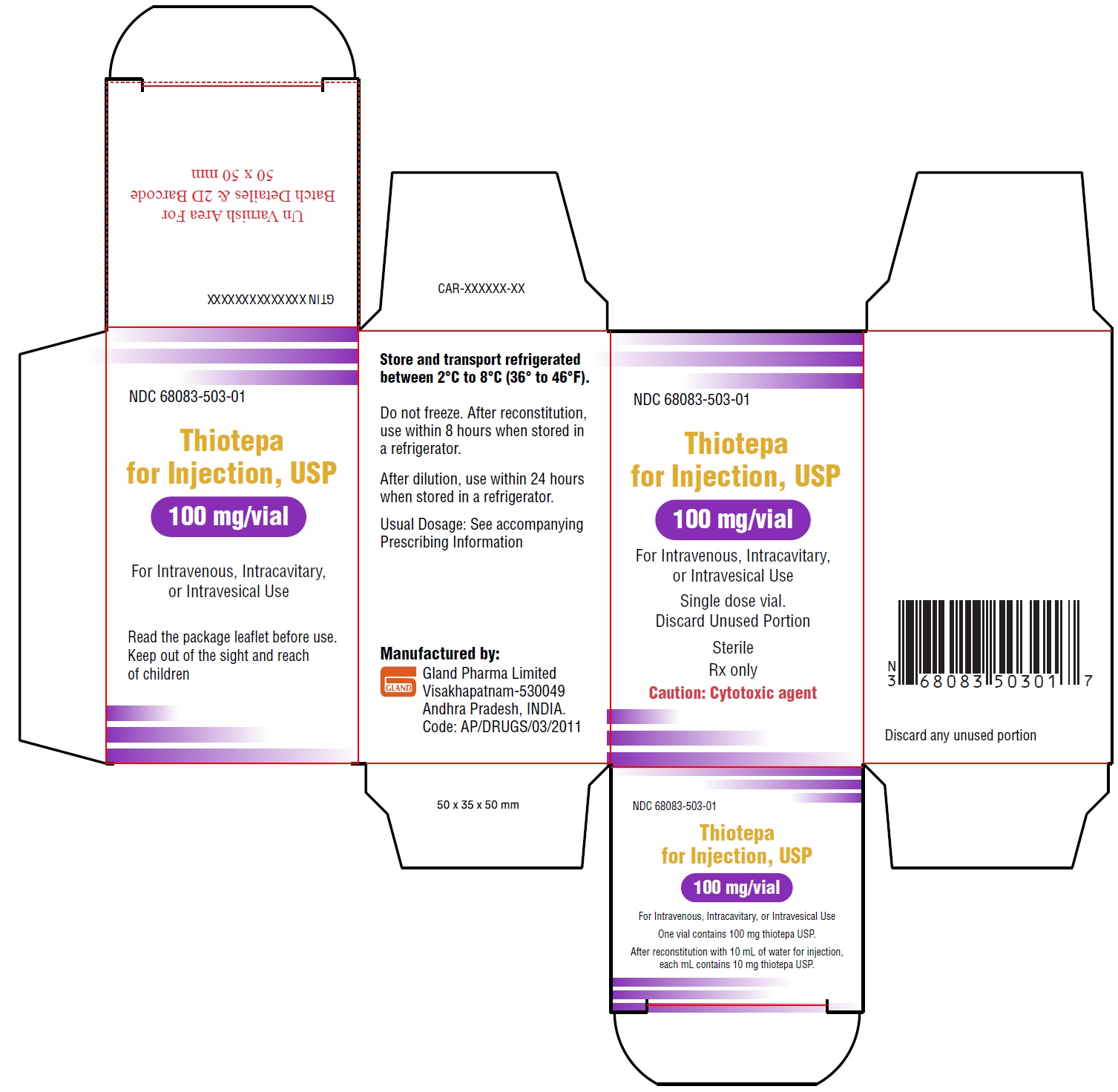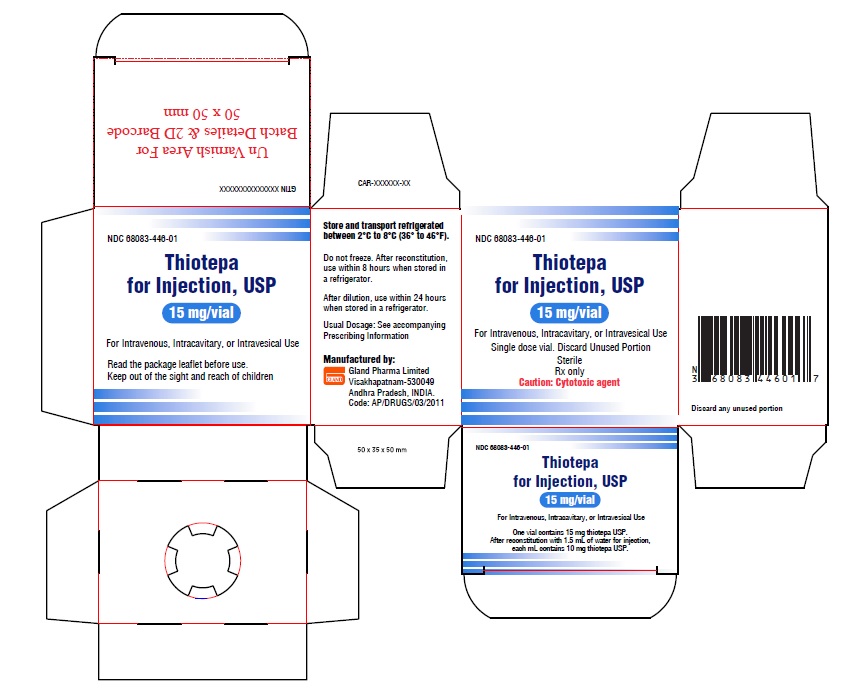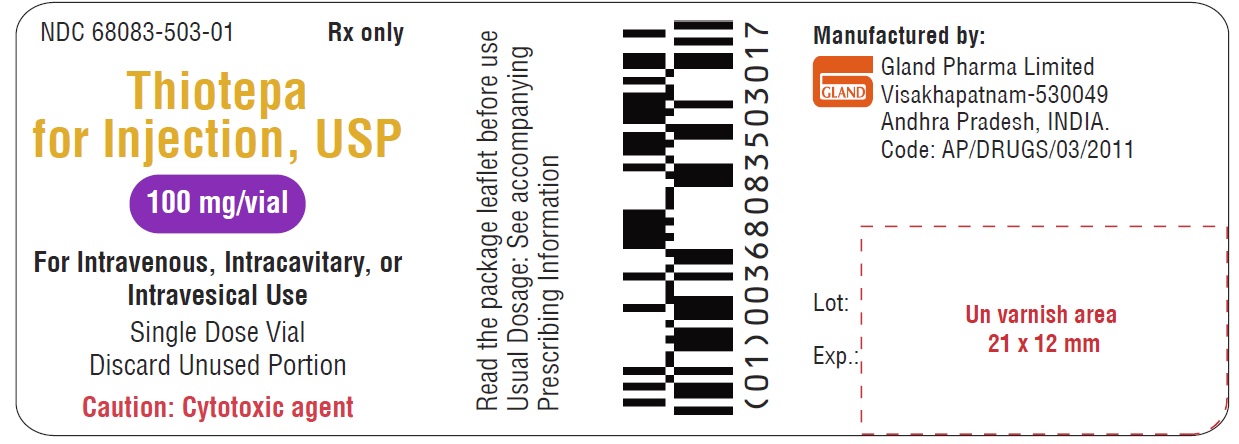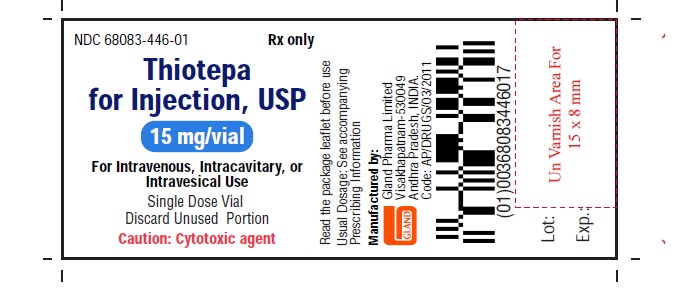 DRUG LABEL: Thiotepa
NDC: 68083-446 | Form: INJECTION, POWDER, LYOPHILIZED, FOR SOLUTION
Manufacturer: Gland Pharma Limited
Category: prescription | Type: Human Prescription Drug Label
Date: 20260123

ACTIVE INGREDIENTS: THIOTEPA 15 mg/1 1
INACTIVE INGREDIENTS: WATER

HIGHLIGHTS OF PRESCRIBING INFORMATION

These highlights do not include all the information needed to use THIOTEPA FOR INJECTION safely and effectively. See full prescribing information for THIOTEPA FOR INJECTION.
THIOTEPA for injection, for intravenous, intracavitary, or intravesical use.
Initial U.S. Approval: 1959

WARNING: SEVERE MYELOSUPPRESSION, CARCINOGENICITY

See full prescribing information for complete boxed warning.

· May cause severe marrow suppression or ablation with resulting infection or bleeding. Monitor hematologic laboratory parameters [see Warnings and Precautions (5.1)]

· Potentially carcinogenic in humans [see Warnings and Precautions (5.7)]

1 INDICATIONS AND USAGE

Thiotepa for injection is an alkylating drug indicated:

• To reduce the risk of graft rejection when used in conjunction with high-dose busulfan and cyclophosphamide as a preparative regimen for allogeneic hematopoietic progenitor (stem) cell transplantation (HSCT) for pediatric patients with class 3 beta-thalassemia. (1.1, 14)

• For treatment of adenocarcinoma of the breast or ovary. (1.2)
• For controlling intracavitary effusions secondary to diffuse or localized neoplastic diseases of various serosal cavities. (1.3)
• For treatment of superficial papillary carcinoma of the urinary bladder. (1.4)

2 DOSAGE AND ADMINISTRATION

• The recommended dose of thiotepa for injection for class 3 beta-thalassemia is two administrations of 5 mg/kg given intravenously approximately 12 hours apart on Day -6 before allogeneic HSCT in conjunction with high-dose busulfan and cyclophosphamide. (2.1)

• The recommended dose of thiotepa for injection for treatment of adenocarcinoma of the breast or ovary is 0.3 to 0.4 mg/kg intravenously. (2.1)
• The recommended dose of thiotepa for injection for treatment of malignant effusions is 0.6 to 0.8 mg/kg intracavitary. (2.1)
• The recommended dose of thiotepa for injection for treatment of superficial papillary carcinoma of the urinary bladder is 60 mg in 30 to 60 mL of Sodium Chloride Injection into the bladder by catheter. (2.1)

3 DOSAGE FORMS AND STRENGTHS

• For injection: 15 mg, lyophilized white powder in single-dose vial for reconstitution. (3)

• For injection: 100 mg, lyophilized white powder in single-dose vial for reconstitution. (3)

4 CONTRAINDICATIONS

• Hypersensitivity to the active substance. (4)
• Concomitant use with live or attenuated vaccines. (4)

5 WARNINGS AND PRECAUTIONS

• Cutaneous toxicity: Cleanse skin at least twice daily through 48 hours after the last dose of thiotepa. (5.3)
• Embryo-Fetal toxicity: Can cause fetal harm. Advise females of reproductive potential of the potential risk to a fetus and to avoid pregnancy. (5.8)

6 ADVERSE REACTIONS

The most common adverse reactions (incidence greater than 10%) were neutropenia, anemia, thrombocytopenia, elevated alanine aminotransferase, elevated aspartate aminotransferase, elevated bilirubin, mucositis, cytomegalovirus infection, hemorrhage, diarrhea, hematuria and rash. (6.1)

To report SUSPECTED ADVERSE REACTIONS, contact Gland Pharma Limited at 866-770-7144 or FDA at 1-800-FDA-1088 or www.fda.gov/medwatch.

8 USE IN SPECIFIC POPULATIONS

• Lactation: Breastfeeding is not recommended. (8.2)
• Moderate or severe renal impairment: Monitor patients more frequently for toxicity. (8.6, 12.2)
• Moderate or severe hepatic impairment: Monitor patients more frequently for toxicity. (8.7, 12.2)

FULL PRESCRIBING INFORMATION

WARNING: SEVERE MYELOSUPPRESSION, CARCINOGENICITY

• Thiotepa may cause severe marrow suppression, and high doses may cause marrow ablation with resulting infection or bleeding. Monitor hematologic laboratory parameters. Hematopoietic progenitor (stem) cell transplantation (HSCT) is required to prevent potentially fatal complications of the prolonged myelosuppression after high doses of thiotepa [see Warnings and Precautions (5.1)]
• Thiotepa should be considered potentially carcinogenic in humans [see Warnings and Precautions (5.7)]

1 INDICATIONS AND USAGE

1.1 Class 3 Beta-Thalassemia

Thiotepa for injection is indicated to reduce the risk of graft rejection when used in conjunction with high-dose busulfan and cyclophosphamide as a preparative regimen for allogeneic hematopoietic progenitor (stem) cell transplantation (HSCT) for pediatric patients with class 3 beta-thalassemia [see Clinical Studies (14)].

1.2 Adenocarcinoma of the Breast or Ovary

Thiotepa for injection is indicated for treatment of adenocarcinoma of the breast or ovary.

1.3 Malignant Effusions

Thiotepa for injection is indicated for controlling intracavitary effusions secondary to diffuse or localized neoplastic diseases of various serosal cavities.

1.4 Superficial Papillary Carcinoma of the Urinary Bladder

Thiotepa for injection is indicated for treatment of superficial papillary carcinoma of the urinary bladder.

2 DOSAGE AND ADMINISTRATION

2.1 Recommended Dosage

Class 3 Beta-Thalassemia
The recommended dose of thiotepa for injection in pediatric patients is two administrations of 5 mg/kg given intravenously approximately 12 hours apart on Day -6 before allogeneic HSCT in conjunction with high-dose busulfan and cyclophosphamide as outlined in Table 1. See Prescribing Information for cyclophosphamide and busulfan for information on these drugs.
Table 1: Dosage Regimen For Allogeneic HSCT In Pediatric Patients With Class 3 Beta-Thalassemia

 | Day prior to transplantation
Treatment | Day -10 | Day -9 | Day -8 | Day -7 | Day -6 | Day -5 | Day -4 | Day -3 | Day -2 | Day -1 | Day 0
Busulfan IV weight-based dose * | ▲ | ▲ | ▲ | ▲
Thiotepa for injection IV 5 mg/kg twice |  |  |  |  | ▲
Cyclophosphamide IV 40 mg/kg/day |  |  |  |  |  | ▲ | ▲ | ▲ | ▲
Stem cell Infusion |  |  |  |  |  |  |  |  |  |  | ▲

*Busulfan IV weight-based dose: 1 mg/kg every 6 hours for patients less than 9 kg; 1.2 mg/kg every 6 hours for patients 9 to 16 kg; 1.1 mg/kg every 6 hours for patients 16.1 to 23 kg; 0.95 mg/kg every 6 hours for patients 23.1 to 34 kg; 0.8 mg/kg every 6 hours for patients more than 34 kg.

Infuse thiotepa for injection via a central venous catheter over 3 hours using an infusion set equipped with a 0.2 micron in-line filter. Prior to and following each infusion, flush the catheter with approximately 5 mL sodium chloride 0.9% solution for injection.
Thiotepa for injection is excreted through the skin of patients receiving high-dose therapy. Take precautions to prevent skin toxicity [see Warnings and Precautions (5.3)].

Adenocarcinoma of the Breast or Ovary

The recommended dose of thiotepa for injection for treatment of adenocarcinoma of the breast or ovary is 0.3 to 0.4 mg/kg intravenously. Doses should be given at 1 to 4 week intervals. Initially the higher dose in the given range is commonly administered. The maintenance dose should be adjusted weekly on the basis of pretreatment control blood counts and subsequent blood counts. Maintenance doses should not be administered more frequently than weekly.

Malignant Effusions

The recommended dose of thiotepa for injection for treatment of malignant effusions is 0.6 to 0.8 mg/kg intracavitary. Administration is usually effected through the same tubing which is used to remove the fluid from the cavity involved. Doses should be given at 1 to 4 week intervals. Initially the higher dose in the given range is commonly administered. The maintenance dose should be adjusted weekly on the basis of pretreatment control blood counts and subsequent blood counts. Maintenance doses should not be administered more frequently than weekly.

Superficial Papillary Carcinoma of the Urinary Bladder

The recommended dose of thiotepa for injection for treatment of superficial papillary carcinoma of the urinary bladder is 60 mg in 30 to 60 mL of Sodium Chloride Injection into the bladder by catheter. The solution should be retained for 2 hours. If the patient finds it impossible to retain 60 mL for 2 hours, the dose may be given in a volume of 30 mL. The patient may be repositioned every 15 minutes for maximum area contact. The usual course of treatment is once a week for 4 weeks. The course may be repeated if necessary, but second and third courses must be given with caution since bone-marrow depression may be increased.

2.2 Preparation Instructions

Thiotepa for injection is a cytotoxic drug. Follow applicable special handling and disposal procedures^1.

Reconstitution

Reconstitute thiotepa for injection 15 mg with 1.5 mL of sterile water for injection. Using a syringe fitted with a needle, aseptically withdraw 1.5 mL of sterile water for injection. Inject the content of the syringe into the vial through the rubber stopper. Remove the syringe and needle, and mix manually by repeated inversions.

Reconstitute thiotepa for injection 100 mg with 10 mL of sterile water for injection. Using a syringe fitted with a needle, aseptically withdraw 10 mL of sterile water for injection. Inject the content of the syringe into the vial through the rubber stopper. Remove the syringe and needle, and mix manually by repeated inversions.

The reconstituted solution is hypotonic and must be diluted in saline prior to administration. Reconstituted solutions, free of visible particulate matter, may occasionally show opalescence; such solutions can still be used for further dilution.

If not used immediately after reconstitution, the product is stable for 8 hours when stored at 2°C to 8°C (36° to 46°F).

Dilution in the infusion bag

Prior to administration, dilute the reconstituted solution further with an appropriate volume of sodium chloride 0.9% solution for injection to obtain a final thiotepa for injection concentration between 0.5 and 1 mg/mL. Dilute thiotepa for injection as recommended in Table 2.

Table 2: Dilution of Thiotepa for Injection in the infusion bag

Calculated Thiotepa for Injection Dose | Dilution Volume (Sodium Chloride 0.9% solution for injection)
Less than 250 mg | Appropriate volume to obtain a final concentration of 0.5 to 1 mg/mL
250 mg to 500 mg | 500 mL or appropriate volume to obtain a final concentration of 0.5 to 1 mg/mL
Greater than 500 mg | 1000 mL or appropriate volume to obtain a final concentration of 0.5 to 1 mg/mL

After dilution the product is stable for 24 hours when stored at 2°C to 8°C (36° to 46°F) and for 4 hours when stored at 25°C (77°F). From a microbiological point of view, the product should be used immediately.
Inspect the diluted solution visually for particulate matter and discoloration prior to administration. Use thiotepa for injection diluted solutions only if free of visible particulate matter. Filter using a 0.2 micron filter prior to administration. Filtering does not alter solution potency

3 DOSAGE FORMS AND STRENGTHS

• For injection, 15 mg, lyophilized white powder in single-dose vial for reconstitution

• For injection, 100 mg, lyophilized white powder in single-dose vial for reconstitution

4 CONTRAINDICATIONS

Thiotepa for injection is contraindicated in:
• Patients with severe hypersensitivity to thiotepa [see Warnings and Precautions (5.2)]
• Concomitant use with live or attenuated vaccines [see Warnings and Precautions (5.4)]

5 WARNINGS AND PRECAUTIONS

5.1 Myelosuppression

The consequence of treatment with high doses of thiotepa together with other chemotherapy at the recommended dose and schedule in the preparative regimen for class 3 beta-thalassemia is profound myelosuppression occurring in all patients. Do not begin the preparative regimen if a stem cell donor is not available. Monitor complete blood counts, and provide supportive care for infections, anemia and thrombocytopenia until there is adequate hematopoietic recovery.

For patients receiving thiotepa for treatment of adenocarcinoma of the breast, adenocarcinoma of the ovary, malignant effusions and superficial papillary carcinoma of the urinary bladder, if the bone marrow has been compromised by prior irradiation or chemotherapy, or is recovering from chemotherapy, the risk of severe myelosuppression with thiotepa may be increased. Perform periodic complete blood counts during the course of treatment with thiotepa. Provide supportive care for infections, bleeding, and symptomatic anemia [see Adverse Reactions (6.1)].

5.2 Hypersensitivity

Clinically significant hypersensitivity reactions, including anaphylaxis, have occurred following administration of thiotepa. If anaphylactic or other clinically significant allergic reaction occurs, discontinue treatment with thiotepa, initiate appropriate therapy, and monitor until signs and symptoms resolve [see Contraindications (4), Adverse Reactions (6.1)].

5.3 Cutaneous Toxicity

Thiotepa and/or its active metabolites may be excreted in part via skin patients receiving high-dose therapy. Treatment with thiotepa may cause skin discoloration, pruritus, blistering, desquamation, and peeling that may be more severe in the groin, axillae, skin folds, in the neck area, and under dressings. Instruct patients to shower or bathe with water at least twice daily through 48 hours after administration of thiotepa. Change occlusive dressing and clean the covered skin at least twice daily through 48 hours after administration of thiotepa. Change bed sheets daily during treatment.
Skin reactions associated with accidental exposure to thiotepa may also occur. Wash the skin thoroughly with soap and water in case thiotepa solution contacts the skin. Flush mucous membranes in case of thiotepa contact with mucous membranes.

5.4 Concomitant Use of Live and Attenuated Vaccines

Do not administer live or attenuated viral or bacterial vaccines to a patient treated with thiotepa until the immunosuppressive effects have resolved.

5.5 Hepatic Veno-Occlusive Disease

Hepatic veno-occlusive disease may occur in patients who have received high-dose thiotepa in conjunction with busulfan and cyclophosphamide [see Adverse Reactions (6.1)]. Monitor by physical examination, serum transaminases and bilirubin daily through BMT Day +28, and provide supportive care to patients who develop hepatic veno-occlusive disease.

5.6 Central Nervous System Toxicity

Fatal encephalopathy has occurred in patients treated with high doses of thiotepa. Other central nervous system toxicities, such as headache, apathy, psychomotor retardation, disorientation, confusion, amnesia, hallucinations, drowsiness, somnolence, seizures, coma, inappropriate behaviour and forgetfulness have been reported to occur in a dose-dependent manner during or shortly after administration of high-dose thiotepa. In pediatric patients treated with thiotepa at the recommended dose in combination with busulfan and cyclophosphamide, 8% developed central nervous system toxicity (seizures and intracranial hemorrhage). Do not exceed the recommended dose of thiotepa. If severe or life-threatening central nervous system toxicity occurs, discontinue administration of thiotepa and provide supportive care.

5.7 Carcinogenicity

Like many alkylating agents, thiotepa has been reported to be carcinogenic when administered to laboratory animals [see Nonclinical Toxicity (13.1)]. Carcinogenicity is shown most clearly in studies using mice, but there is some evidence of carcinogenicity in man. There is an increased risk of a secondary malignancy with use of thiotepa.

5.8 Embryo-Fetal Toxicity

Based on the mechanism of action and findings in animals, thiotepa can cause fetal harm when administered to a pregnant woman. There are no adequate and well-controlled studies of thiotepa in pregnant women. Thiotepa given by the intraperitoneal (IP) route was teratogenic in mice at doses ≥ 1 mg/kg (3.2 mg/m^2), approximately 8-fold less than the maximum recommended human therapeutic dose (0.8 mg/kg, 27 mg/m^2), based on body-surface area. Thiotepa given by the IP route was teratogenic in rats at doses ≥ 3 mg/kg (21 mg/m^2), approximately equal to the maximum recommended human therapeutic dose, based on body-surface area. Thiotepa was lethal to rabbit fetuses at a dose of 3 mg/kg (41 mg/m^2), approximately two times the maximum recommended human therapeutic dose based on body-surface area.
Advise pregnant women of the potential risk to the fetus [see Use in Specific Populations (8.1,8.3)]. Advise females of reproductive potential to use highly effective contraception during and after treatment with thiotepa for at least 6 months after therapy. Advise males of reproductive potential to use effective contraception during and after treatment with thiotepa for at least 1 year after therapy [see Use in Specific Populations (8.1, 8.3)].

6 ADVERSE REACTIONS

The following clinically significant adverse reactions are described elsewhere in the labeling:

· Myelosuppression [see Warnings and Precautions (5.1)]

· Infection [see Warnings and Precautions (5.1)]

· Hypersensitivity [see Warnings and Precautions (5.2)]

· Cutaneous Toxicity [see Warnings and Precautions (5.3)]

· Hepatic Veno-Occlusive Disease [see Warnings and Precautions (5.5)]

· Central Nervous System Toxicity [see Warnings and Precautions (5.6)]

· Carcinogenicity [see Warnings and Precautions (5.7)]

6.1 Clinical Trials Experience

Because clinical trials are conducted under widely varying conditions, adverse reaction rates observed in the clinical trials of a drug cannot be directly compared to rates in the clinical trials of another drug and may not reflect the rates observed in practice.

Adverse Reactions With the Preparative Regimen for Class 3 Beta-Thalassemia
The safety of thiotepa was evaluated by retrospective analysis of 76 pediatric patients with class 3 beta-thalassemia who underwent allogeneic hematopoietic progenitor (stem) cell transplantation (HSCT) using busulfan and cyclophosphamide with thiotepa (n=25) or without thiotepa (n=51) [see Clinical Studies (14)]. Adverse reactions were abstracted retrospectively from the medical records.
Serious adverse events that occurred in the thiotepa-treated and control cohort were, respectively: gastrointestinal hemorrhage (4% vs 2%), pneumonia (4% vs 0), seizure (4% vs 2%), subarachnoid hemorrhage (4% vs 0) and venoocclusive disease (4% vs 2%). By 90 days after HSCT, grades 2 to 4 acute graft-versus-host disease was observed in 7 (28%) patients in the thiotepa cohort and in 13 (26%) patients in the control cohort. By 1-year after transplantation, chronic graft-versus-host disease was observed in 8 (35%) of 23 evaluable patients in the thiotepa cohort, and 7 (14%) of 49 evaluable patients in the control cohort.
Adverse reactions occurring in at least 5% of patients treated with thiotepa from start of the preparative regimen through 30 days after transplantation are shown in Table 3.

Table 3: Common Adverse Reactions (>5%) Occurring Through 30 Days After Transplantation In Patients With Class 3 Beta-Thalassemia Using Busulfan And Cyclophosphamide With Or Without Thiotepa in the Preparative Regimen

 | Preparative Regimen of Busulfan and Cyclophosphamide
 | With Thiotepa N=25 patients (%) |  | Without Thiotepa N=51 patients (%)
Adverse Reaction | Any Grade | Grade 3-5^1 | Any Grade | Grade 3-5^1
Mucositis^2 | 16 (64%) | 4 (16%) | 22 (43%) | 1 (2%)
Cytomegalovirus Infection | 12 (48%) | 0 | 15 (29%) | 0
Hemorrhage^3 | 7 (28%) | 2 (8%) | 12 (24%) | 3 (6%)
Diarrhea | 6 (24%) | 0 | 7 (14%) | 2 (4%)
Hematuria^4 | 5 (20%) | 0 | 10 (20%) | 3 (6%)
Rash^5 | 3 (12%) | 0 | 11 (22%) | 0
Intracranial Hemorrhage^6 | 2 (8%) | 1 (4%) | 0 | 0
Pseudomonas Infection | 2 (8%) | 0 | 0 | 0

^1Severe, life-threatening or fatal

^2Mucositis includes mouth hemorrhage, mucosal inflammation and stomatitis
^3Hemorrhage includes all hemorrhage terms
^4Hematuria includes cystitis hemorrhagic and hematuria
^5Rash includes dermatitis exfoliative, palmar erythema, rash, rash maculo-papular, rash pruritic and skin toxicity
^6Hemorrhage Intracranial includes hemorrhage intracranial and subarachnoid hemorrhage
All patients in the Thiotepa-treated and control cohorts developed profound cytopenias, including neutropenia, anemia, thrombocytopenia. Table 4 shows the selected chemistry abnormalities that occurred from start of the preparative regimen through 30 days after transplantation.
Table 4: Selected Laboratory Abnormalities Occurring Through 30 Days After Transplantation In Patients With Class 3 Beta-Thalassemia Using Busulfan And Cyclophosphamide With Or Without Thiotepa in the Preparative Regimen

 | Preparative Regimen of Busulfan and Cyclophosphamide
 | With Thiotepa N=25 patients (%) |  | Without Thiotepa N=51 patients (%)
Adverse Reaction | Any Grade | Grade 3-4 | Any Grade | Grade 3-4
Elevated alanine aminotransferase | 22 (88%) | 6 (24%) | 49 (96%) | 14 (27%)
Elevated aspartate aminotransferase | 20 (80%) | 4 (16%) | 45 (88%) | 9 (18%)
Elevated total bilirubin | 20 (80%) | 4 (16%) | 39 (77%) | 2 (4%)

Adverse Reactions with Treatment of adenocarcinoma of the breast, adenocarcinoma of the ovary, malignant effusions and superficial papillary carcinoma of the urinary bladder

Gastrointestinal: Nausea, vomiting, abdominal pain, anorexia.

General: Fatigue, weakness. Febrile reaction and discharge from a subcutaneous lesion may occur as the result of breakdown of tumor tissue.

Hypersensitivity Reactions: Allergic reactions - rash, urticaria, laryngeal edema, asthma, anaphylactic shock, wheezing.

Local Reactions: Contact dermatitis, pain at the injection site.

Neurologic: Dizziness, headache, blurred vision.

Renal: Dysuria, urinary retention, chemical cystitis or hemorrhagic cystitis.

Reproductive: Amenorrhea, interference with spermatogenesis.

Respiratory: Prolonged apnea has been reported when succinylcholine was administered prior to surgery, following combined use of thiotepa and other anticancer agents. It was theorized that this was caused by decrease of pseudocholinesterase activity caused by the anticancer drugs.

Skin: Dermatitis, alopecia. Skin depigmentation has been reported following topical use.

Special Senses: Conjunctivitis.

6.2 Postmarketing Experience

Because these reactions are reported voluntarily from a population of uncertain size, it is not always possible to reliably estimate their frequency or establish a causal relationship to drug exposure.

The following adverse reactions have been identified during post approval use of thiotepa in preparative regimens prior to allogeneic or autologous hematopoietic progenitor (stem) cell transplantation (HSCT) in adult and pediatric patients.

Blood and lymphatic system disorders: Febrile bone marrow aplasia.

Cardiac disorders: Bradycardia, cardiac failure congestive, cardio-respiratory arrest, pericardial effusion, pericarditis, right ventricular hypertrophy.

Congenital, familial and genetic disorders: Aplasia.

Ear and labyrinth disorders: Deafness.

Eye disorders: Blindness, eyelid ptosis, papilledema, strabismus.

Gastrointestinal disorders: Ascites, dysphagia, enterocolitis, gastritis, palatal disorder.

General disorders and administration site conditions: Device related infection, gait disturbance, malaise, multi-organ failure, pain.

Hepatobiliary disorders: Hepatomegaly.

Immune system disorders: Bone marrow transplant rejection, immunosuppression.

Infections and infestations: Acute sinusitis, bronchopulmonary aspergillosis, candida sepsis, enterococcal infection, Epstein-Barr virus infection, Escherichia sepsis, Fusarium infection, gastroenteritis, infection, lower respiratory tract infection fungal, lower respiratory tract infection viral, parainfluenza virus infection, Pneumonia legionella, relapsing fever, respiratory tract infection, sepsis, septic shock, Staphylococcal bacteremia, Staphylococcal infection, systemic candida, urinary tract infection.

Injury, poisoning and procedural complications: Refractoriness to platelet transfusion, subdural hematoma.

Investigations: Coagulation test abnormal, hemoglobin decreased, Klebsiella test positive, nuclear magnetic resonance imaging brain abnormal, transaminases increased, weight increased.

Metabolism and nutrition disorders: Hyponatremia.

Neoplasms benign, malignant and unspecified (incl. cysts and polyps): Breast cancer metastatic, central nervous system lymphoma, leukemia recurrent, lymphoma, malignant neoplasm progression, metastatic neoplasm, post transplant lymphoproliferative disorder.

Nervous system disorders: Aphasia, brain injury, bulbar palsy, central nervous system lesion, cerebral microangiopathy, cerebral ventricle dilatation, cerebrovascular accident, cognitive disorder, convulsion, coordination abnormal, encephalitis, encephalopathy, hemiplegia, hypotonia, leukoencephalopathy, memory impairment, motor dysfunction, neurotoxicity, quadriparesis, speech disorder, tremor, VIIth nerve paralysis, white matter lesion.

Psychiatric disorders: Delirium, depression, disorientation, suicidal ideation.

Renal and urinary disorders: Renal failure, nephropathy toxic.

Respiratory, thoracic and mediastinal disorders: Acute respiratory distress, aspiration, dyspnea exertional, interstitial lung disease, lung disorder, pneumonitis, pulmonary arteriopathy, pulmonary sepsis, pulmonary veno-occlusive disease, respiratory distress, respiratory failure, pulmonary hypertension.

Skin and subcutaneous tissue disorders: Stevens-Johnson syndrome and toxic epidermal necrolysis.

Vascular disorders: Capillary leak syndrome.

7 DRUG INTERACTIONS

7.1 Effect of Cytochrome CYP3A Inhibitors and Inducers

In vitro studies suggest that thiotepa is metabolized by CYP3A4 and CYP2B6 to its active metabolite TEPA. Avoid coadministration of strong CYP3A4 inhibitors (e.g., itraconazole, clarithromycin, ritonavir) and strong CYP3A4 inducers (e.g., rifampin, phenytoin) with thiotepa due to the potential effects on efficacy and toxicity [see Clinical Pharmacology (12.2)]. Consider alternative medications with no or minimal potential to inhibit or induce CYP3A4. If concomitant use of strong CYP3A4 modulators cannot be avoided, closely monitor for adverse drug reactions.

7.2 Effect of Thiotepa on Cytochrome CYP2B6 Substrates

In vitro studies suggest that thiotepa inhibits CYP2B6. Thiotepa may increase the exposure of drugs that are substrates of CYP2B6 in patients; however, the clinical relevance of this in vitro interaction is unknown [see Clinical Pharmacology (12.2)].

The administration of thiotepa with cyclophosphamide in patients reduces the conversion of cyclophosphamide to the active metabolite, 4-hydroxycyclophosphamide; the effect appears sequence dependent with a greater reduction in the conversion to 4-hydroxycyclophosphamide when thiotepa is administered 1.5 hours prior to the intravenous administration of cyclophosphamide compared to administration of thiotepa after intravenous cyclophosphamide [see Clinical Pharmacology (12.2)]. The reduction in 4-hydroxycyclophosphamide levels may potentially reduce efficacy of cyclophosphamide treatment.

8 USE IN SPECIFIC POPULATIONS

8.1 Pregnancy

Risk Summary

Thiotepa can cause fetal harm when administered to a pregnant woman based on findings from animals and the drug’s mechanism of action [see Clinical Pharmacology (12.1)]. Limited available data with thiotepa use in pregnant women are insufficient to inform a drug-associated risk of major birth defects and miscarriage. In animal reproduction studies, administration of thiotepa to pregnant mice and rats during organogenesis produced teratogenic effects (neural tube defects and malformations of the skeletal system of the fetus) at doses approximately 0.125 and 1 times, respectively, the maximum recommended human daily dose on a mg/m^2 basis. Thiotepa was lethal to rabbit fetuses at approximately 2 times the maximum recommended human therapeutic dose based on body-surface area [see Data]. Consider the benefits and risks of thiotepa for the mother and possible risks to the fetus when prescribing thiotepa to a pregnant woman.

The estimated background risk of major birth defects and miscarriage for the indicated population is unknown. In the U.S. general population, the estimated background risk of major birth defects and miscarriage in clinically recognized pregnancies is 2 to 4% and 15 to 20%, respectively.

Data

Animal Data

Thiotepa given by the IP route in mice at doses ≥ 1 mg/kg (3.2 mg/m^2), approximately 8-fold less than the maximum recommended human therapeutic dose based on body-surface area, and in rats at doses ≥ 3 mg/kg (21 mg/m^2), approximately equal to the maximum recommended human therapeutic dose based on body-surface area, resulted in various malformations including neural tube defects, omphalocele, renal agenesis, atresia ani, limb and digit defects, cleft palate, micrognathia, other skeletal anomalies in the skull, vertebrae and ribs, and reduced skeletal ossification. Thiotepa was lethal to rabbit fetuses at a dose of 3 mg/kg (41 mg/m^2), approximately 2 times the maximum recommended human therapeutic dose based on body-surface area.

8.2 Lactation

Risk Summary

There is no information regarding the presence of thiotepa in human milk, the effects on the breastfed infant, or the effects on milk production.

Because of the potential for serious adverse reactions, including the potential for tumorigenicity shown for thiotepa in animal studies, advise patients not to breastfeed during thiotepa treatment.

8.3 Females and Males of Reproductive Potential

Pregnancy testing

Thiotepa can cause fetal harm when administered to a pregnant female. Verify the pregnancy status of females of reproductive potential prior to initiating thiotepa therapy.

Contraception

Females

Advise females of reproductive potential to avoid pregnancy during thiotepa treatment and for at least 6 months after the final dose of thiotepa. Advise females to immediately report pregnancy [see Use in Specific Populations (8.1)].

Males

Thiotepa may damage spermatozoa and testicular tissue, resulting in possible genetic abnormalities. Males with female sexual partners of reproductive potential should use effective contraception during thiotepa treatment and for at least 1 year after the final dose of thiotepa [see Nonclinical Toxicology (13.1)].

Infertility

Based on nonclinical findings, male and female fertility may be compromised by treatment with thiotepa. Inform male patients about the possibility of sperm conservation before the start of therapy [see Nonclinical Toxicology (13.1)].

8.4 Pediatric Use

The safety and effectiveness of thiotepa for prevention of graft rejection in pediatric patients undergoing allogeneic HSCT for class 3 beta-thalassemia was established in one prospective study and one retrospective study [see Clinical Studies (14)] that included 1 infant (1 month to 1 year), 23 children (2 to 11 years) and 13 adolescents (12 to 16 years) who received thiotepa as part of their preparative regimen. Safety and effectiveness of thiotepa in neonates have not been established.

Safety and effectiveness of thiotepa for treatment of adenocarcinoma of the breast, adenocarcinoma of the ovary, malignant effusions and superficial papillary carcinoma of the urinary bladder in pediatric patients have not been established.

8.5 Geriatric Use

The safety and effectiveness of thiotepa as a preparative regimen prior to allogeneic hematopoietic progenitor (stem) cell transplantation (HSCT) for patients with class 3 beta-thalassemia have not been established in geriatric patients. Clinical studies of thiotepa for this indication did not include subjects aged 65 and over.

Clinical studies of thiotepa for treatment of adenocarcinoma of the breast, adenocarcinoma of the ovary, malignant effusions and superficial papillary carcinoma of the urinary bladder did not include sufficient numbers of subjects aged 65 and over to determine whether elderly subjects respond differently from younger subjects, and other reported clinical experience has not identified differences in responses between the elderly and younger patients. In general, dose selection for an elderly patient should be cautious, usually starting at the low end of the dosing range, reflecting the greater frequency of decreasing hepatic, renal or cardiac function, and of concomitant disease or other drug therapy.

8.6 Renal Impairment

In patients with moderate (creatinine clearance (CLcr) of 30 mL/min to 59 mL/min) renal impairment, decreased renal excretion may result in increased plasma levels of thiotepa and TEPA [see Clinical Pharmacology (12.2)]. This may result in increased toxicity. Monitor patients with moderate to severe (CLcr < 30 mL/min) renal impairment for signs and symptoms of toxicity following treatment with thiotepa for an extended period of time.

8.7 Hepatic Impairment

Thiotepa is extensively metabolized in the liver. Patients with moderate (bilirubin levels greater than 1.5 times to 3 times the upper limit of normal and any AST) hepatic impairment may have increased plasma levels of thiotepa [see Clinical Pharmacology (12.2)]. This may result in toxicity. Monitor patients with moderate to severe (bilirubin levels greater than 3 times upper limit of normal and any AST) hepatic impairment for signs and symptoms of toxicity following treatment with thiotepa for an extended period of time.

10 OVERDOSE

There is no experience with overdoses of thiotepa. The most important adverse reactions expected in case of overdose are myeloablation and pancytopenia [see Nonclinical Toxicology (13.2)]. There is no known antidote for thiotepa. Monitor the hematological status closely and provide vigorous supportive measures as medically indicated.

11 DESCRIPTION

Thiotepa is an alkylating agent. Thiotepa for injection, USP is supplied as a non-pyrogenic, sterile lyophilized white powder for intravenous, intracavitary, or intravesical use after reconstitution and dilution.

Thiotepa for injection, USP is available in a single-dose vial containing:
• 15 mg thiotepa. After reconstitution with 1.5 mL of water for injection, each mL contains 10 mg thiotepa.
• 100 mg thiotepa. After reconstitution with 10 mL of water for injection, each mL contains 10 mg thiotepa.

Thiotepa is a synthetic product with antitumor activity. The chemical name for thiotepa is Tris(1-aziridinyl)phosphine sulfide. Thiotepa has the following structural formula:

Thiotepa, USP has the molecular formula C6H12N3PS, and a molecular weight of 189.22, and it appears as fine, white crystalline flakes, with a melting range of 52°C to 57°C. It is soluble in water and organic solvents. When reconstituted with sterile water for injection, the resulting solution has a pH of approximately 5.5 to 7.5. Thiotepa is unstable in acid medium.

12 CLINICAL PHARMACOLOGY

12.1 Mechanism of Action

Thiotepa is a cytotoxic agent of the polyfunctional type, related chemically and pharmacologically to the nitrogen mustard. The radiomimetic action of thiotepa is believed to occur through the release of ethyleneimine radicals which, like irradiation, disrupt the bonds of DNA. One of the principle bond disruptions is initiated by alkylation of guanine at the N-7 position, which severs the linkage between the purine base and the sugar and liberates alkylated guanines.

12.2 Pharmacokinetics

Absorption

Thiotepa reached maximal concentrations close to the end infusion following an intravenous infusion.

Distribution

The binding of thiotepa to plasma proteins is approximately 10% to 20%. The mean volume of distribution (% coefficient of variation) of thiotepa was 30 L/m^2 (44%) or 1.2 L/kg (47%) following a single intravenous infusion of thiotepa at a dose of 5 mg/kg over 3 hours in pediatric population. In adults administered intravenous thiotepa between 20 mg to 250 mg/m^2 as an intravenous bolus or infusion up to 4 hours, the mean volume of distribution of thiotepa ranged from 1.0 L/kg (30%) to 1.9 L/kg (17%).

Elimination

Following a single intravenous infusion over 3 hours of thiotepa at a dose of 5 mg/kg in pediatric population, the estimated mean (% coefficient of variation) clearance of thiotepa was 0.58 L/hr/kg (60%) or 13.8 L/hr/m2 (52%). The mean terminal elimination half-life was 1.7 hours (64%) for thiotepa and 4 hours (29%) for its major active metabolite, N,N',N''-triethylenephosphoramide (TEPA) in pediatric population. In adults administered intravenous thiotepa between 20 mg to 250 mg/m^2 as an intravenous bolus or infusion up to 4 hours, the mean thiotepa clearance ranged from 14.6 L/hr/m^2 (23%) to 27.9 L/hr/m^2 (69%). In adult population, the mean terminal elimination half-life ranged from 1.4 hours (7%) to 3.7 hours (14%) for thiotepa and from 4.9 hours to 17.6 hours (20%) for TEPA.

Metabolism

Thiotepa undergoes hepatic metabolism. In vitro data suggests that CYP3A4 and CYP2B6 may be responsible for the metabolism of thiotepa to TEPA, a major active metabolite.

Excretion

In adult and pediatric patients, urinary excretion of thiotepa accounted for less than 2% of the dose and TEPA accounted for 11% or less of the dose.

Specific Populations

Hepatic Impairment

The clearance of thiotepa following a single thiotepa dose of 5 mg/kg in pediatric population with mild hepatic impairment was similar to the clearance observed in patients with normal liver function administered thiotepa. The exposure (as measured by area under the curve (AUC)) of thiotepa increased by 1.6-fold and 1.8-fold following administration of multiple thiotepa doses of 7 mg/kg administered every 2 days with cyclophosphamide in two adult patients who had liver metastases with moderate hepatic impairment compared to the exposure observed in one patient with normal hepatic function. The effect of severe hepatic impairment on thiotepa exposure is unknown.

Renal Impairment

The exposure (as measured by AUC) of thiotepa increased by 1.4-fold and TEPA increased by 2.6-fold following administration of multiple doses of 120 mg/m^2/day in one patient with moderate renal impairment (CLcr = 38 mL/min) administered cyclophosphamide plus thiotepa plus carboplatin, compared to exposure of thiotepa in patients with normal renal function. The effects of severe renal impairment or end-stage renal disease on thiotepa exposure are unknown.

Drug Interactions

The clinical relevance of in vitro inhibition of the cytochrome P450 enzymes described below is unknown, but it cannot be excluded that the systemic exposure of thiotepa or medicinal products that are substrates for these enzymes may be affected with concomitant administration with thiotepa.

Effect of Cytochrome P450 Modulators on Thiotepa

In vitro data demonstrates that CYP3A4 and CYP2B6 inhibitors decrease the metabolism of thiotepa [see Drug Interactions (7.1)].

Effect of Thiotepa on Cytochrome P450 2B6

In vitro data demonstrates that thiotepa inhibits CYP2B6.

Effect of Thiotepa on Cyclophosphamide

The administration of thiotepa 1.5 hours prior to intravenous cyclophosphamide in patients administered cyclophosphamide plus thiotepa plus carboplatin decreased the AUC of 4-hydroxycyclophosphamide by 26% and maximal concentrations of 4-hydroxycyclophosphamide by 62%, compared to administration of cyclophosphamide prior to thiotepa.

13 NONCLINICAL TOXICOLOGY

13.1 Carcinogenesis, Mutagenesis, Impairment of Fertility

In mice, repeated intraperitoneal (IP) administration of thiotepa (1.15 or 2.3 mg/kg three times per week for 52 or 43 weeks, respectively) produced a significant increase in the combined incidence of squamous-cell carcinomas of the skin, preputial gland, and ear canal, and combined incidence of lymphoma and lymphocytic leukemia. In other studies in mice, repeated IP administration of thiotepa (4 or 8 mg/kg three times per week for 4 weeks followed by a 20 week observation period or 1.8 mg/kg three times per week for 4 weeks followed by a 35 week observation period) resulted in an increased incidence of lung tumors. In rats, repeated IP administration of thiotepa (0.7 or 1.4 mg/kg three times per week for 52 or 34 weeks, respectively) produced significant increases in the incidence of squamous-cell carcinomas of the skin or ear canal, combined hematopoietic neoplasms, and uterine adenocarcinomas. Thiotepa given intravenously (IV) to rats (1 mg/kg once per week for 52 weeks) produced an increased incidence of malignant tumors (abdominal cavity sarcoma, lymphosarcoma myelosis, seminoma, fibrosarcoma, salivary gland hemangioendothelioma, mammary sarcoma, pheochromocytoma) and benign tumors.

The lowest reported carcinogenic dose in mice (1.15 mg/kg, 3.68 mg/m^2) is approximately 7-fold less than the maximum recommended human therapeutic dose based on body-surface area. The lowest reported carcinogenic dose in rats (0.7 mg/kg, 4.9 mg/m^2) is approximately 6-fold less than the maximum recommended human therapeutic dose based on body-surface area.

Thiotepa was mutagenic in in vitro assays in Salmonella typhimurium, E coli, Chinese hamster lung and human lymphocytes. Chromosomal aberrations and sister chromatid exchanges were observed in vitro with thiotepa in bean root tips, human lymphocytes, Chinese hamster lung, and monkey lymphocytes.

Mutations were observed with oral thiotepa in mouse at doses > 2.5 mg/kg (8 mg/m^2). The mouse micronucleus test was positive with intraperitoneal administration of > 1 mg/kg (3.2 mg/m^2). Other positive in vivo chromosomal aberration or mutation assays included Drosophila melanogaster, Chinese hamster marrow, murine marrow, monkey lymphocyte, and murine germ cell.

Thiotepa impaired fertility in male mice at oral or intraperitoneal doses ≥ 0.7 mg/kg (2.24 mg/m^2), approximately 12-fold less than the maximum recommended human therapeutic dose based on body-surface area. Thiotepa (0.5 mg) inhibited implantation in female rats when instilled into the uterine cavity. Thiotepa interfered with spermatogenesis in mice at IP doses ≥ 0.5 mg/kg (1.6 mg/m^2), approximately 17-fold less than the maximum recommended human therapeutic dose based on body-surface area. Thiotepa interfered with spermatogenesis in hamsters at an IP dose of 1 mg/kg (4.1 mg/m^2), approximately 7-fold less than the maximum recommended human therapeutic dose based on body-surface area.

14 CLINICAL STUDIES

Thiotepa was evaluated in a retrospective study of pediatric patients with class 3 beta-thalassemia who underwent allogeneic hematopoietic progenitor (stem) cell transplantation (HSCT) from a human leukocyte antigen (HLA)-identical sibling donor. Twenty-five patients (10 male and 15 female) of median age 10 years (range, 5-16 years) were treated with intravenous busulfan at weight-based dosing from Day -10 to Day -7 pretransplant [see Table 1]), intravenous thiotepa 5 mg/kg twice on Day -6, intravenous cyclophosphamide 40 mg/kg/day on Day -5 to Day -2, and marrow infusion on Day 0. All patients had also received precytoreduction with hydroxyurea, azathioprine and fludarabine prior to start of the preparative regimen.
Efficacy was based on the incidence of graft rejection (primary or late rejection). The incidence of graft rejection in these 25 patients using thiotepa was 0% (95% CI: [0, 0.12]). Of the 51 patients who received the same preparative regimen, historically, without thiotepa, the incidence of graft rejection reported was 25.5% (95% CI: [0.13, 0.37]).

15 REFERENCES

1. OSHA Hazardous Drugs. OSHA. [Accessed from http://www.osha.gov/SLTC/hazardousdrugs/index.html].

16 HOW SUPPLIED/STORAGE AND HANDLING

16.1 How Supplied

Thiotepa for Injection, USP is supplied as Unit carton with one single-dose Type I clear glass vial. The vial stopper is not made with natural rubber latex.

Thiotepa for Injection, USP 15 mg

One vial contains 15 mg thiotepa (NDC 68083-446-01).

Thiotepa for Injection, USP 100 mg

One vial contains 100 mg thiotepa (NDC 68083-503-01).

16.2 Storage and Handling

Thiotepa for injection, USP vials must be stored and transported refrigerated at 2°C to 8°C (36° to 46°F). Do not freeze. Discard Unused Portion.

Thiotepa for injection, USP is a cytotoxic drug. Follow applicable special handling and disposal procedures^1.

17 PATIENT COUNSELING INFORMATION

Hypersensitivity

Counsel patients on the signs and symptoms of hypersensitivity and to seek immediate emergency assistance if they develop any of these signs and symptoms [see Warnings and Precautions (5.2)].

Myelosuppression
Inform patients of the possibility of developing low blood cell counts and the need for hematopoietic progenitor cell infusion. Instruct patients to immediately report to their healthcare provider if bleeding or fever occurs [see Warnings and Precautions (5.1)].

Females and Males of Reproductive Potential

Thiotepa for injection can cause fetal harm. Advise females receiving thiotepa for injection to avoid pregnancy during thiotepa for injection treatment and for at least 6 months after the final dose of thiotepa for injection [see Warnings and Precautions (5.8)].

Advise males with female sexual partners of reproductive potential to use effective contraception during thiotepa for injection treatment and for at least 1 year after the final dose of thiotepa for injection[see Use in Specific Populations (8.3)].

Advise females to report pregnancy immediately [see Warnings and Precautions (5.8)].

Advise patients that thiotepa for injection can produce infertility. Inform male patients about the possibility of sperm conservation before the start of therapy [see Use in Specific Populations (8.3)].

Lactation

Advise patients to avoid breastfeeding while receiving thiotepa for injection [see Use in Specific Populations (8.2)].

Secondary malignancies

Inform patients that thiotepa for injection can increase the risk of secondary malignancy [see Warnings and Precautions (5.7)].

Manufactured by:
Gland Pharma Limited
Visakhapatnam-530049

Andhra Pradesh, India.

Revised: 01/2026

PACKAGE LABEL.PRINCIPAL DISPLAY PANEL - 15 mg - Vial Label

NDC 68083-446-01 Rx only

Thiotepa

for Injection, USP
15 mg/vial

For Intravenous, Intracavitary, or

Intravesical use

Single Dose Vial

Discard Unused Portion

Caution: Cytotoxic agent

PACKAGE LABEL – PRINCIPAL DISPLAY PANEL – 15 mg - Carton Label

NDC 68083-446-01

Thiotepa

for Injection, USP

15 mg/vial
For Intravenous, Intracavitary, or Intravesical use
Single dose vial. Discard Unused Portion
Sterile
Rx only
Caution: Cytotoxic agent

PACKAGE LABEL.PRINCIPAL DISPLAY PANEL - 100 mg - Vial Label

NDC 68083-503-01 Rx only

Thiotepa

for Injection, USP
100 mg/vial

For Intravenous, Intracavitary, or

Intravesical use

Single Dose Vial

Discard Unused Portion

Caution: Cytotoxic agent

PACKAGE LABEL.PRINCIPAL DISPLAY PANEL - 100 mg - Carton Label

NDC 68083-503-01

Thiotepa

for Injection, USP

100 mg/vial
For Intravenous, Intracavitary, or
Intravesical use
Single dose vial.

Discard Unused Portion

Sterile
Rx only
Caution: Cytotoxic agent